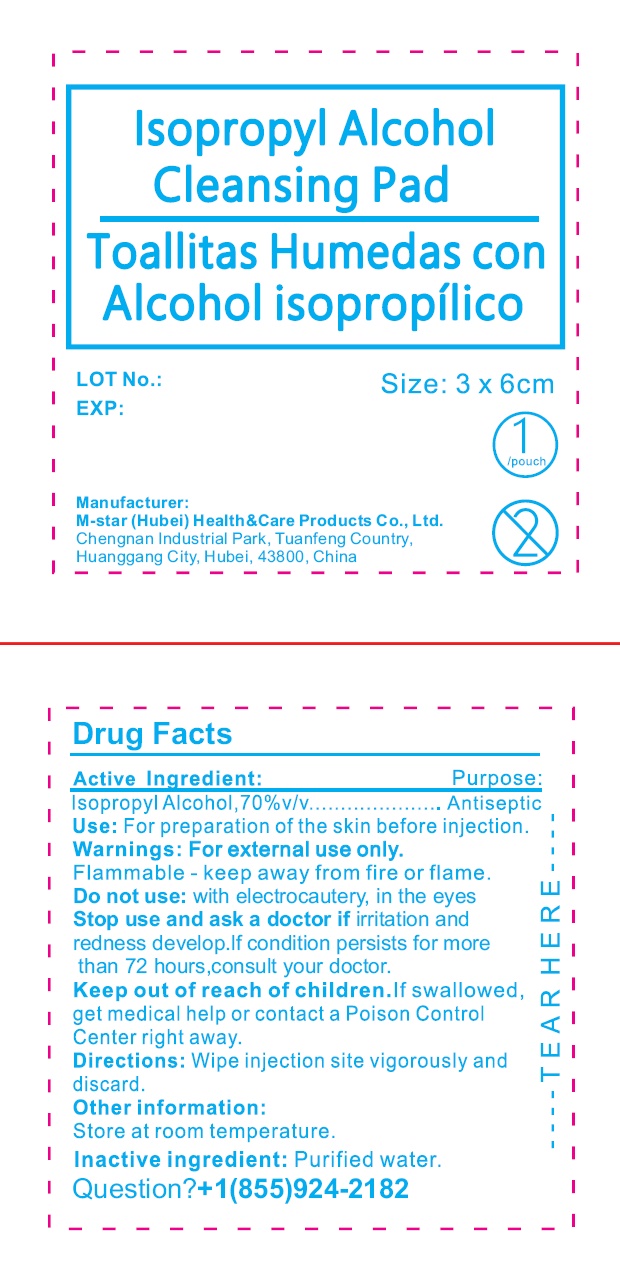 DRUG LABEL: Isopropyl Alcohol Cleansing Pad TOALLITAS HUMEDAS CON ALCOHOL ISOPROPILICO
NDC: 84219-000 | Form: CLOTH
Manufacturer: M-star (Hubei) Health&Care Products Co., Ltd.
Category: otc | Type: HUMAN OTC DRUG LABEL
Date: 20240401

ACTIVE INGREDIENTS: ISOPROPYL ALCOHOL 70 g/100 g
INACTIVE INGREDIENTS: WATER

Isopropyl Alcohol Cleansing Pad TOALLITAS HUMEDAS CON ALCOHOL ISOPROPILICO

Active ingredient:

Isopropyl Alcohol, 70% v/v

Purpose:

Antiseptic

Use:

For preparation of the skin before injection.

Warnings:

For external use only.

Flammable - keep away from fire or flame.

Do not use:

with electrocautery, in the eyes

Stop use and ask a doctor if

irritation and redness develop.If condition persists for more than 72 hours,consult your doctor.

Keep out of reach of children.

If swallowed, get medical help or contact a Poison Control Center right away.

Directions:

Wipe injection site vigorously and discard.

Other information:

Store at room temperature

Inactive ingredient:

Purified water.

Questions?

+1(855)924-2182